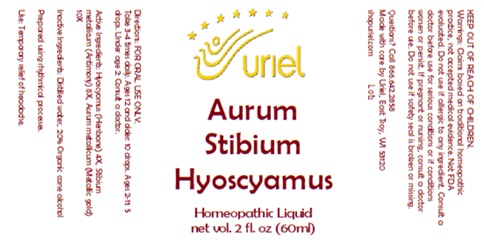 DRUG LABEL: Aurum Stibium Hyoscyamus
NDC: 48951-1403 | Form: LIQUID
Manufacturer: URIEL PHARMACY INC.
Category: homeopathic | Type: HUMAN OTC DRUG LABEL
Date: 20250902

ACTIVE INGREDIENTS: HYOSCYAMUS NIGER LEAF 4 [hp_X]/1 1; ANTIMONY 8 [hp_X]/1 1; GOLD 10 [hp_X]/1 1
INACTIVE INGREDIENTS: WATER; SUCROSE

Aurum Stibium Hyoscyamus

INDICATIONS AND USAGE

Directions: FOR ORAL USE ONLY.

DOSAGE AND ADMINISTRATION

Take 3-4 times daily. Ages 12 and older: 10 drops. Ages 2-11: 5 drops. Under age 2: Consult a doctor.

ACTIVE INGREDIENT

Active Ingredients: Hyoscyamus (Henbane) 4X, Stibium metallicum (Antimony) 8X, Aurum metallicum (Metallic gold) 10X

Inactive Ingredients: Distilled water, 20% Organic cane alcohol

Prepared using rhythmical processes.

PURPOSE

Use: Temporary relief of headache.

KEEP OUT OF REACH OF CHILDREN.

WARNINGS

Warnings: Claims based on traditional homeopathic practice, not accepted medical evidence. Not FDA evaluated. Do not use if allergic to any ingredient. Consult a doctor before use for serious conditions or if conditions worsen or persist. If pregnant or nursing consult a doctor before use. Do not use if safety seal is broken or missing.

Questions? Call 866.642.2858
Made with care by Uriel, East Troy, WI 53120
shopuriel.com